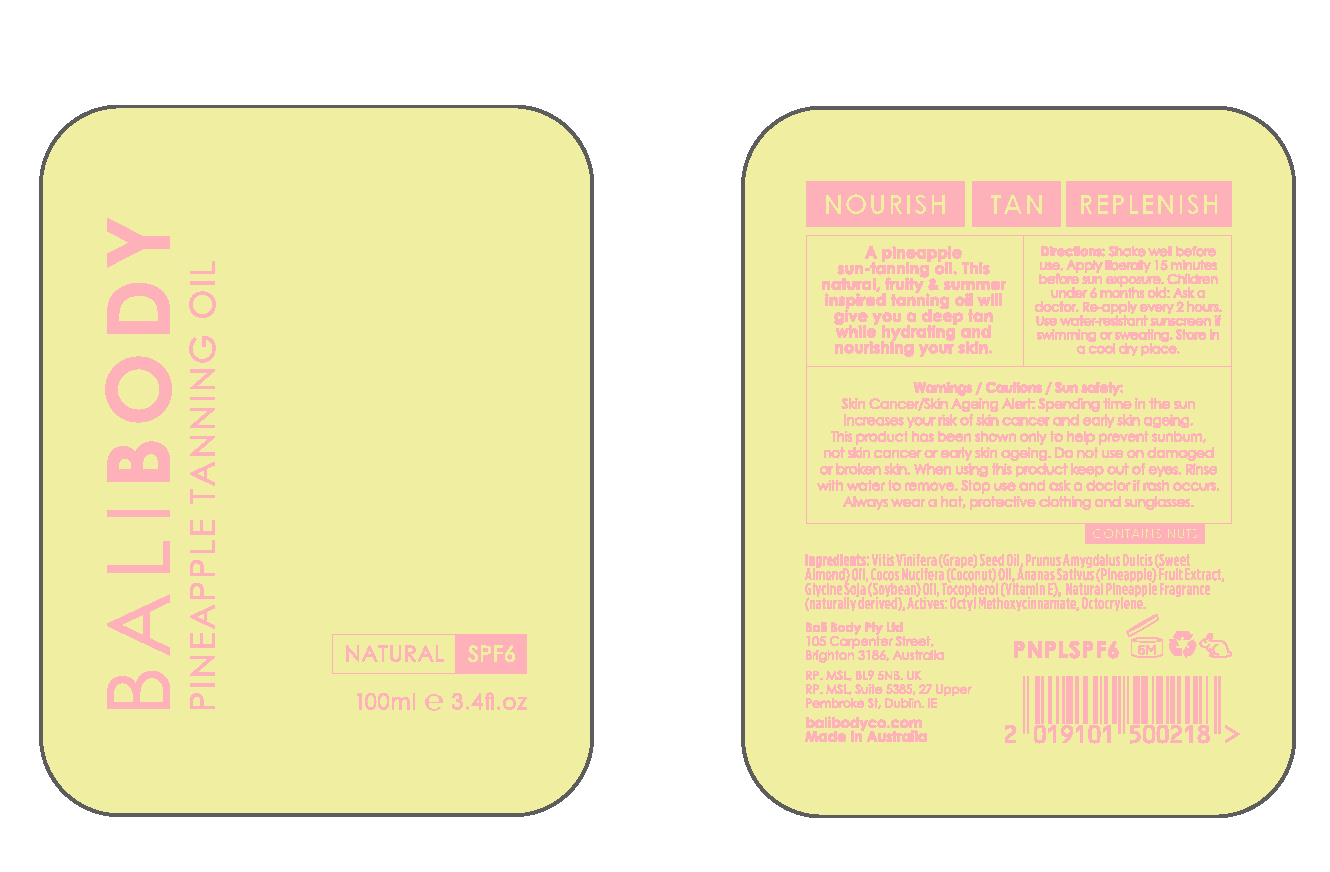 DRUG LABEL: Bali Body SPF Pineapple Tanning Oil SPF 6
NDC: 70630-1801 | Form: OIL
Manufacturer: Bali Body Pty Ltd
Category: otc | Type: HUMAN OTC DRUG LABEL
Date: 20191031

ACTIVE INGREDIENTS: OCTOCRYLENE 2.5 mg/100 mL; OCTINOXATE 2.5 mg/100 mL
INACTIVE INGREDIENTS: .ALPHA.-TOCOPHEROL; SOYBEAN OIL; PINEAPPLE; COCONUT OIL; ALMOND OIL; GRAPE SEED OIL

Bali Body Pineapple Tanning Oil SPF 6

ACTIVE INGREDIENT

Octinoxate 2.5%

Octocrylene 2.5%

Keep out of reach of children.

PURPOSE

A tanning and body oil.

Provides SPF 6 protection.

INDICATIONS AND USAGE

Shake well before use. Apply liberaly 15 minutes before sun exposure.

Children under 6 months: Ask a doctor.

Reapply every 2 hours.

Use water-resistant sunscreen if swimming or sweating.

Store in a cool dry place.

INACTIVE INGREDIENT

- Grape seed oil;
- Coconut oil;
- Soybean oil;
- Sweet almond oil;
- Pineapple; and
- Vitamin E.

WARNINGS

Skin Cancer/Skin Aging Alert: Spending time in the sun increases your risk of skin cancer and early skin aging.

This product has ben shown only to help prevent sunburn, not skin cancer or early skin aging.

Do not use on damaged or broken skin.

When using this product keep out of eyes. Rinse with water to remove.

Stop use and ask a doctor if rash occurs.

Always wear a hat, protective clothing and sunglasses.

DOSAGE AND ADMINISTRATION

Apply liberally 15 minutes before sun exposure.